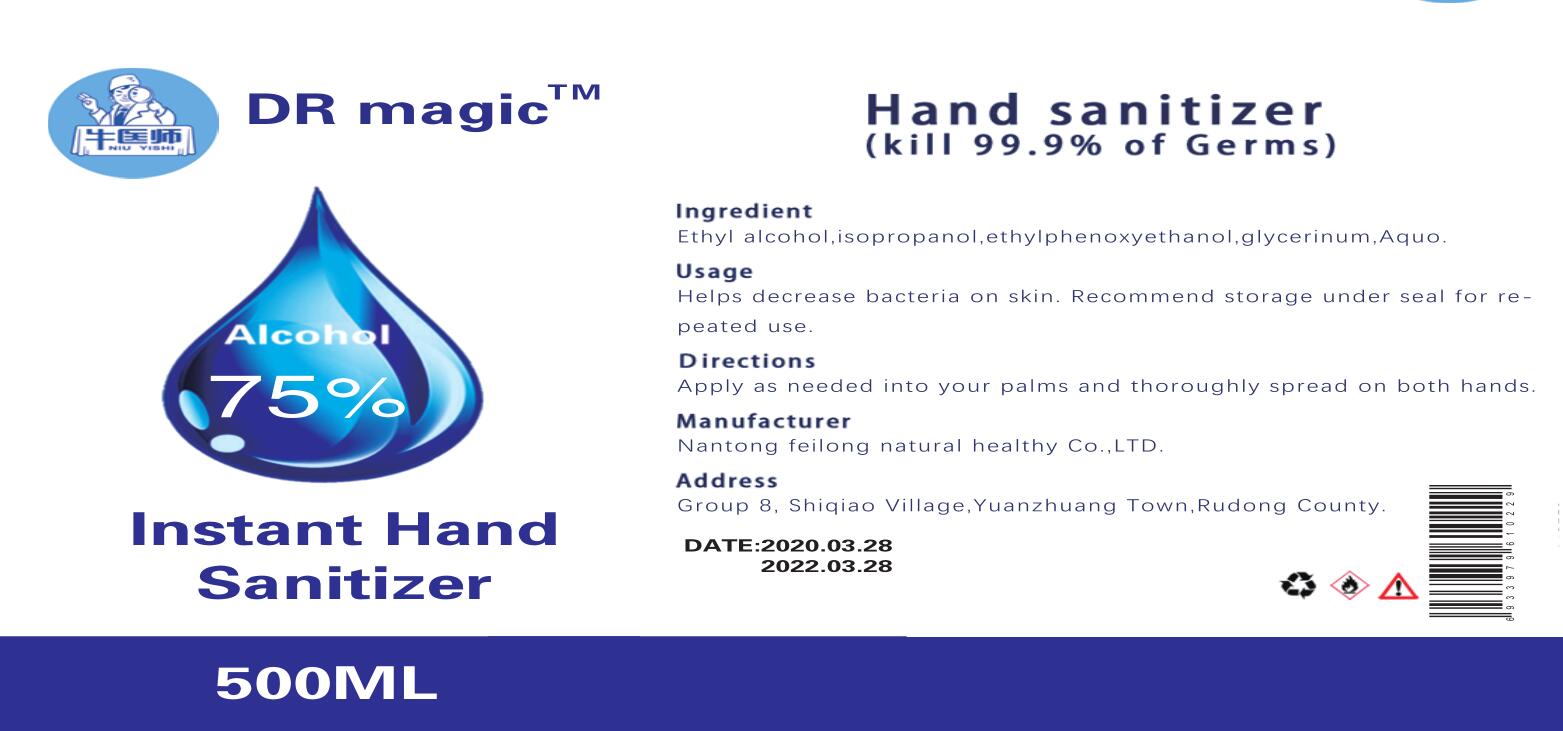 DRUG LABEL: Instant Hand Sanitizer
NDC: 55447-001 | Form: LIQUID
Manufacturer: Nan tong Feilong Natural Healthy Co.,LTD
Category: otc | Type: HUMAN OTC DRUG LABEL
Date: 20200413

ACTIVE INGREDIENTS: ALCOHOL 375 mL/500 mL
INACTIVE INGREDIENTS: GLYCERIN; ISOPROPYL ALCOHOL; WATER; 2-(2-ETHYLHEXYLOXY)ETHANOL

INACTIVE INGREDIENT

Ethyl alcohol,iso propanol,ethylphenoxyethanol,glycerinum,Aquo.

INDICATIONS AND USAGE

Helps decrease bacteria on skin. Recommend storage under seal for repeated use

keep out of reach of children

PURPOSE

Disinfection
Sterilization
No Rinseing

WARNINGS

keep away from the fire source

DOSAGE AND ADMINISTRATION

Apply as needed into your palms and thoroughly spread on both hands.